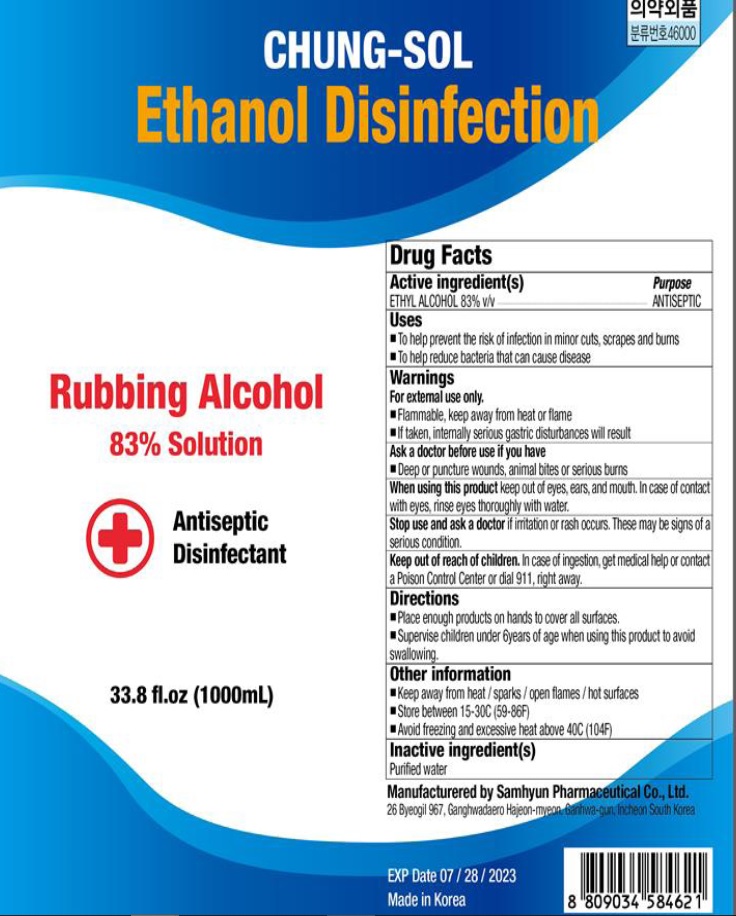 DRUG LABEL: CHUNG SOL DISINFECTION ETHANOL
NDC: 75765-030 | Form: SPRAY
Manufacturer: Samhyun pharma
Category: otc | Type: HUMAN OTC DRUG LABEL
Date: 20200720

ACTIVE INGREDIENTS: ALCOHOL 830 mL/1000 mL
INACTIVE INGREDIENTS: Water

ACTIVE INGREDIENT

Ethanol 83% v/v

INACTIVE INGREDIENT

Purified water

PURPOSE

ANTISEPTIC

WARNINGS

For external use only.
■ Flammable, keep away from heat or flame
■ If taken, internally serious gastric disturbances will result
--------------------------------------------------------------------------------------------------------
Ask a doctor before use if you have
■ Deep or puncture wounds, animal bites or serious burns
--------------------------------------------------------------------------------------------------------
When using this product keep out of eyes, ears, and mouth. In case of contact with eyes, rinse eyes thoroughly with water.
--------------------------------------------------------------------------------------------------------
Stop use and ask a doctor if irritation or rash occurs. These may be signs of a serious condition.

KEEP OUT OF REACH OF CHILDREN

If swallowed, get medical help or contact a Poison Control Center right away.

Uses

■ To help prevent the risk of infection in minor cuts, scrapes and burns
■ To help reduce bacteria that can cause disease

Directions

■ Place enough products on hands to cover all surfaces.
■ Supervise children under 6years of age when using this product to avoid swallowing.

Other information

■ Keep away from heat / sparks / open flames / hot surfaces
■ Store between 15-30C (59-86F)
■ Avoid freezing and excessive heat above 40C (104F)